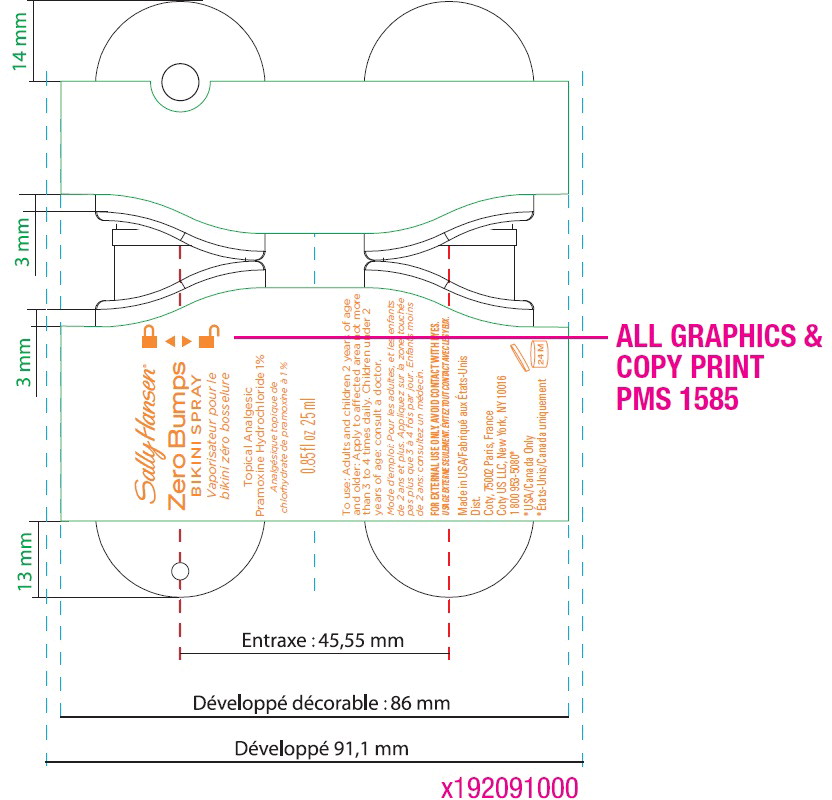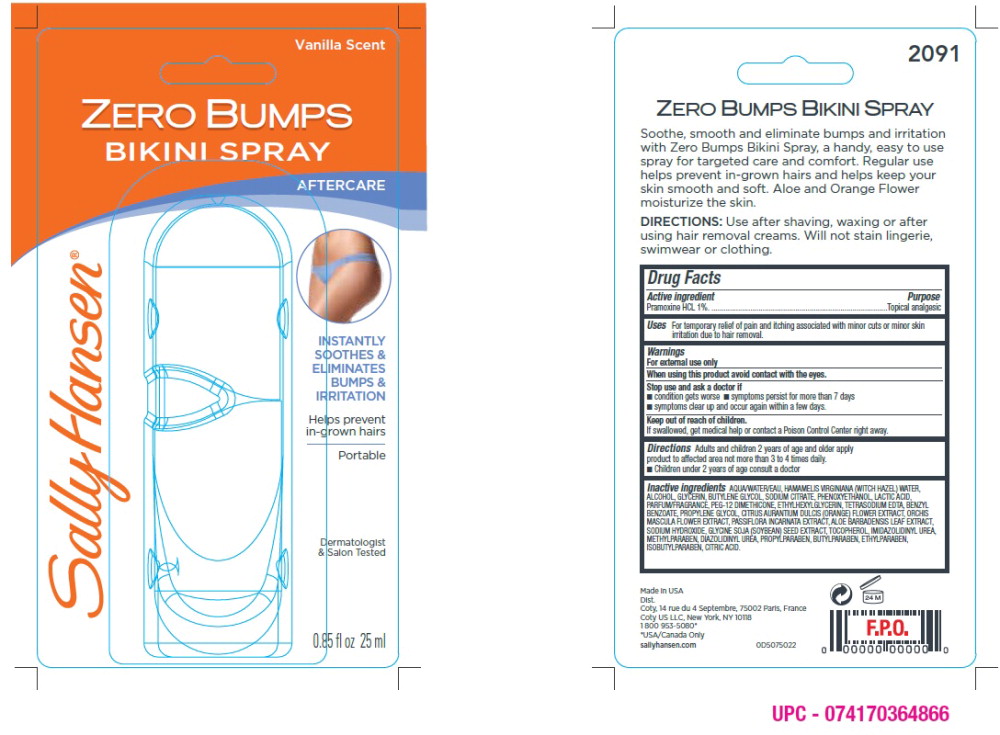 DRUG LABEL: Sally Hansen Zero bump bikini
NDC: 66184-160 | Form: SPRAY
Manufacturer: Coty US LLC
Category: otc | Type: HUMAN OTC DRUG LABEL
Date: 20211019

ACTIVE INGREDIENTS: PRAMOXINE HYDROCHLORIDE 10 mg/1 mL
INACTIVE INGREDIENTS: HAMAMELIS VIRGINIANA FLOWER WATER; ETHYLHEXYLGLYCERIN; .ALPHA.-TOCOPHEROL ACETATE, DL-; EDETATE SODIUM TETRAHYDRATE; BENZYL BENZOATE; CITRUS AURANTIUM FLOWER; ALOE VERA LEAF; METHYLPARABEN; PROPYLENE GLYCOL; ORCHIS MASCULA FLOWER; PASSIFLORA INCARNATA FLOWER; SODIUM HYDROXIDE; N-(3,4-BIS(HYDROXYMETHYL)-2,5-DIOXO-4-IMIDAZOLIDINYL)-N,N'-BIS(HYDROXYMETHYL)UREA; ISOBUTYLPARABEN; WATER; GLYCERIN; SODIUM CITRATE, UNSPECIFIED FORM; PHENOXYETHANOL; LACTIC ACID, DL-; PEG-12 DIMETHICONE (300 CST); SOYBEAN OIL; BUTYLENE GLYCOL; .BETA.-TOCOPHEROL; DIAZOLIDINYL UREA; PROPYLPARABEN; BUTYLPARABEN; ETHYLPARABEN; CITRIC ACID ACETATE

zero bumps bikini spray

Drug Facts

Active Ingredient | Purpose
Pamoxine Hcl 1% | Topical Analgesic

Purpose

Topical Analgesic

Stop use and ask a doctor if

- Condition gets worse
- symptoms persist for more than 7 days
- symptoms clear up and occur again with a few days

Warnings

- For external use only
- When using this product avoid contact with the eyes

Keep out of reach of children

If swallowed, get medical help or contact a poison control center right away.

Directions

- Adults and children 2 years of age and older apply product to affected area not more than 3 to 4 times daily.
- Children under 2 years of age consult a doctor
- Use after shaving, waxing or after using hair removal creams. Will not stain lingerie, swimwear or clothing.

Inactive ingredients

AQUA/WATER/EAU, HAMAMELIS VIRGINIANA (WITCH HAZEL) WATER,
ALCOHOL, GLYCERIN, BUTYLENE GLYCOL, SODIUM CITRATE, PHENOXYETHANOL, LACTIC ACID,
PARFUM/FRAGRANCE, PEG-12 DIMETHICONE, ETHYLHEXYLGLYCERIN, TETRASODIUM EDTA, BENZYL
BENZOATE, PROPYLENE GLYCOL, CITRUS AURANTIUM DULCIS (ORANGE) FLOWER EXTRACT, ORCHIS
MASCULA FLOWER EXTRACT, PASSIFLORA INCARNATA EXTRACT, ALOE BARBADENSIS LEAF EXTRACT,
SODIUM HYDROXIDE, GLYCINE SOJA (SOYBEAN) SEED EXTRACT, TOCOPHEROL, IMIDAZOLIDINYL UREA,
METHYLPARABEN, DIAZOLIDINYL UREA, PROPYLPARABEN, BUTYLPARABEN, ETHYLPARABEN,
ISOBUTYLPARABEN, CITRIC ACID

Uses

For temporary relief of pain and itching associated with minor cuts or minor skin irritation due to hair removal.